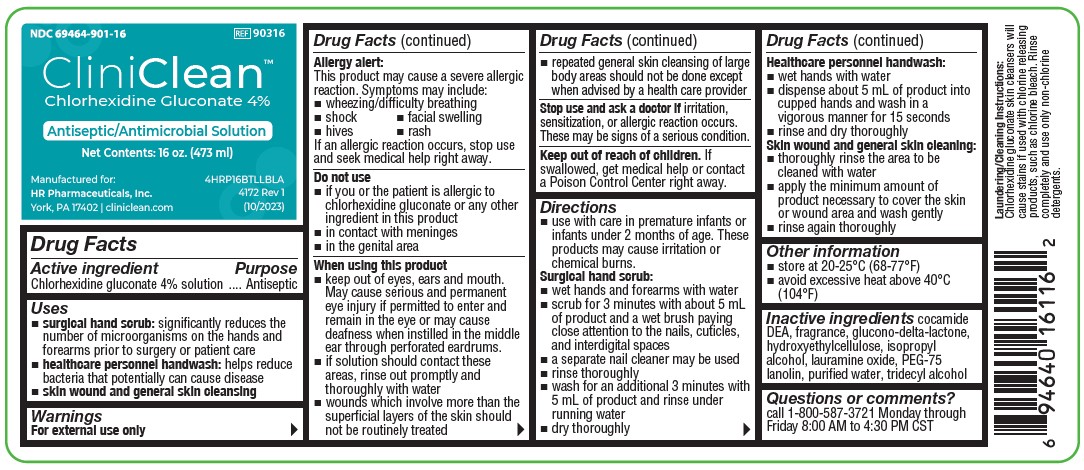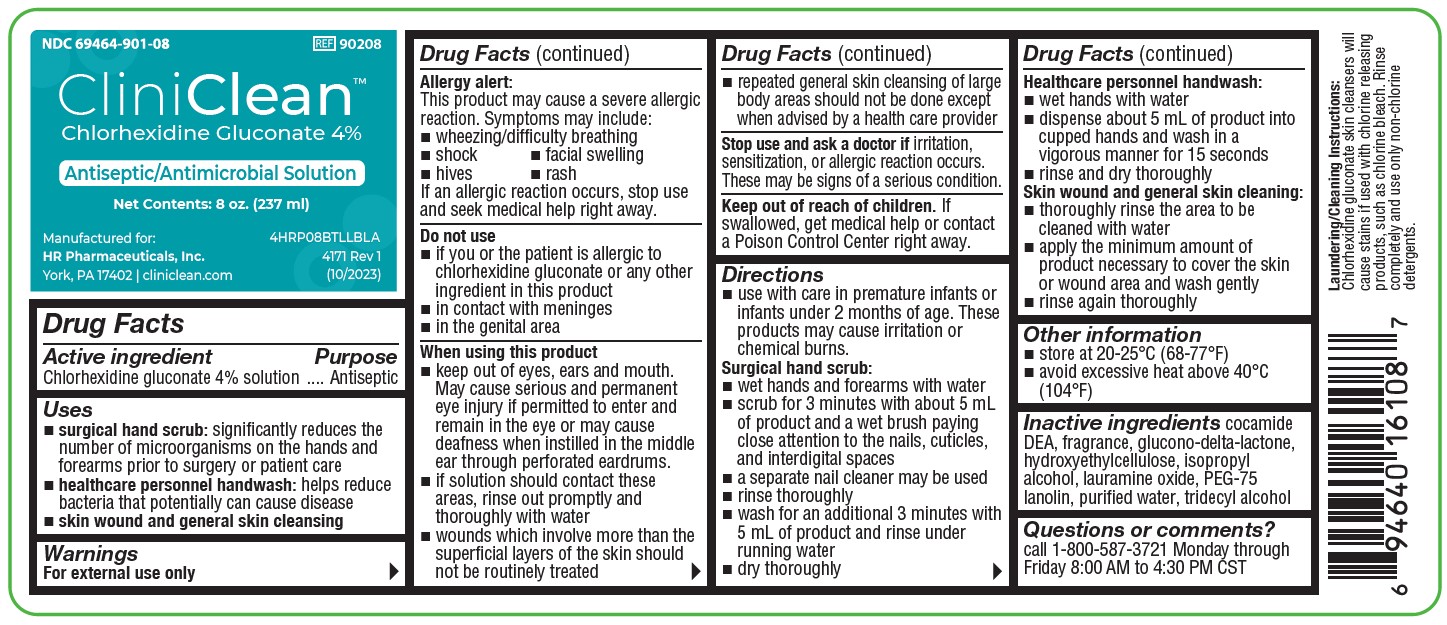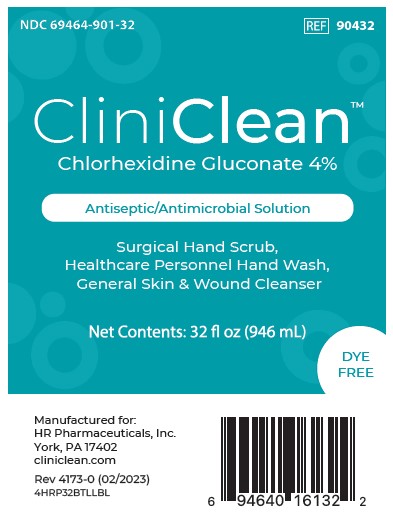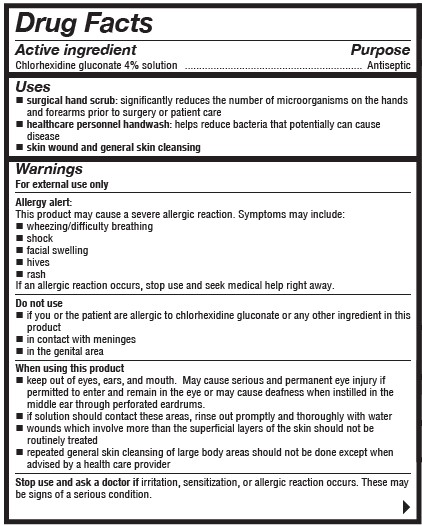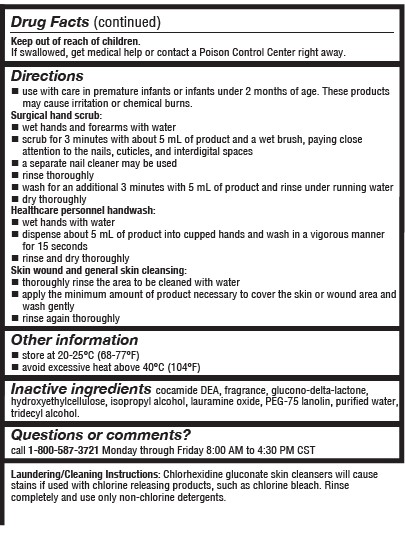 DRUG LABEL: CliniClean
NDC: 69464-901 | Form: SOLUTION
Manufacturer: HR Pharmaceuticals, Inc.
Category: otc | Type: HUMAN OTC DRUG LABEL
Date: 20251216

ACTIVE INGREDIENTS: CHLORHEXIDINE GLUCONATE 4 g/100 mL
INACTIVE INGREDIENTS: GLUCONOLACTONE; PEG-75 LANOLIN; TRIDECYL ALCOHOL; COCO DIETHANOLAMIDE; HYDROXYETHYL CELLULOSE (2000 CPS AT 1%); ISOPROPYL ALCOHOL; WATER; LAURAMINE OXIDE

4% HR Pharma 16oz, & 32oz
COMP 8oz

ACTIVE INGREDIENT

Chlorhexidine gluconate 4% Solution

Purpose

Antiseptic

Uses

- surgical hand scrub: significantly reduces the number of microorganisms on the hands and forearms prior to surgery or patient care
- healthcare personnel handwash: helps reduce bacteria that potentially can cause disease
- skin wound and general cleansing

Warnings

For external use only

Allergy alert:

This product may cause a severe allergic reaction. Symptoms may include:

- wheezing/difficulty breathing
- shock
- facial swelling
- hives
- rash

If an allergic reaction occurs, stop use and seek medical help right away.

Do not use

- if you or the patient is allergic to chlorhexidine gluconate or any other ingredient in this product
- in contact with meninges
- in the genital area

When using this product

- keep out of eyes, ears, and mouth. May cause serious and permanent eye injury if permitted to enter and remain in the eye or may cause deafness when instilled in the middle ear through perforated eardrums.
- if solution should contact these areas, rinse out promptly and thoroughly with water
- wound which involve more than the superficial layers of the skin should not be routinely treated
- repeated general skin cleansing of large body areas should not be done except when advised by a health care provider

Stop use and ask a doctor

if irritation, sensitization, or allergic reaction occurs. These may be signs of a serious condition.

Keep out of reach of children

If swallowed, get medical help or contact a Poison Control Center right away.

Direction

- use with care in premature infants or infants under 2 months of age. These products may cause irritation or chemical burns.

Surgical hand scrub:

- wet hands and forearms with water
- scrub for 3 minutes with about 5 mL of product and a wet brush paying close attention to the nails, cuticles, and interdigital spaces
- a separate nail cleaner may be used
- rinse throughly
- wash for an additional 3 minutes with 5 mL of product and rinse under running water
- dry thoroughly

Healthcare personnel handwash:

- wet hands with water
- dispense about 5 mL of product into cupped hands and wash in a vigorous manner for about 15 seconds
- rinse and dry thoroughly

Skin wound and general skin cleansing:

- thoroughly rinse the area to be cleaned with water
- apply the minimum amount of product necessary to cover the skin or wound area and wash gently
- rinse again thoroughly

other information

- store at 20-25 ºC (68-77 ºF)
- avoid excessive heat above 40 ºC (104 ºF)

Inactive ingredients

cocamide DEA, fragrance, glucono-delta-lactone, hydroxyethylcellulose, isopropyl alcohol, lauramine oxide, PEG-75 lanolin, purified water, tridecyl alcohol

Questions or comments?

call 1-800-587-3721 Monday through Friday 8:00 AM to 4:30 PM CST

Laundry/Cleaning Instrucations

Chlorhexidine gluconate skin cleansers will cause stains if used with chlorine releasing products, such as chlorine bleach. Rinse completely and use only non-chlorine detergents.

Packaging

NDC 69464-901-08

REF 90208

CliniClean

Chlorhexidine Gluconate 4%

Antiseptic/Antimicrobial Solution

Surgical Hand Scrub, Healthcare Personnel Hand Wash, General Skin & Wound Cleanser

Net Contents: 8 fl oz (237 mL)

DYE FREE

Manufactured for:

HR Pharmaceutials, Inc.

York, PA 17402

cliniclean.com

4171 Rev 1

(10/2023)

4HRP08BTLLBLA

NDC 69464-901-16

REF 90316

CliniClean

Chlorhexidine Gluconate 4%

Antiseptic/Antimicrobial Solution

Surgical Hand Scrub, Healthcare Personnel Hand Wash, General Skin & Wound Cleanser

Net Contents: 16 fl oz (473 mL)

DYE FREE

Manufactured for:

HR Pharmaceutials, Inc.

York, PA 17402

cliniclean.com

4172 Rev 1

(10/2023)

4HRP16BTLLBLA

NDC 69464-901-32

REF 90432

CliniClean

Chlorhexidine Gluconate 4%

Antiseptic/Antimicrobial Solution

Surgical Hand Scrub, Healthcare Personnel Hand Wash, General Skin & Wound Cleanser

Net Contents: 32 fl oz (946 mL)

DYE FREE

Manufactured for:

HR Pharmaceutials, Inc.

York, PA 17402

cliniclean.com

Rev 4171-0 (02/2023)

4HRP32BTLLBL